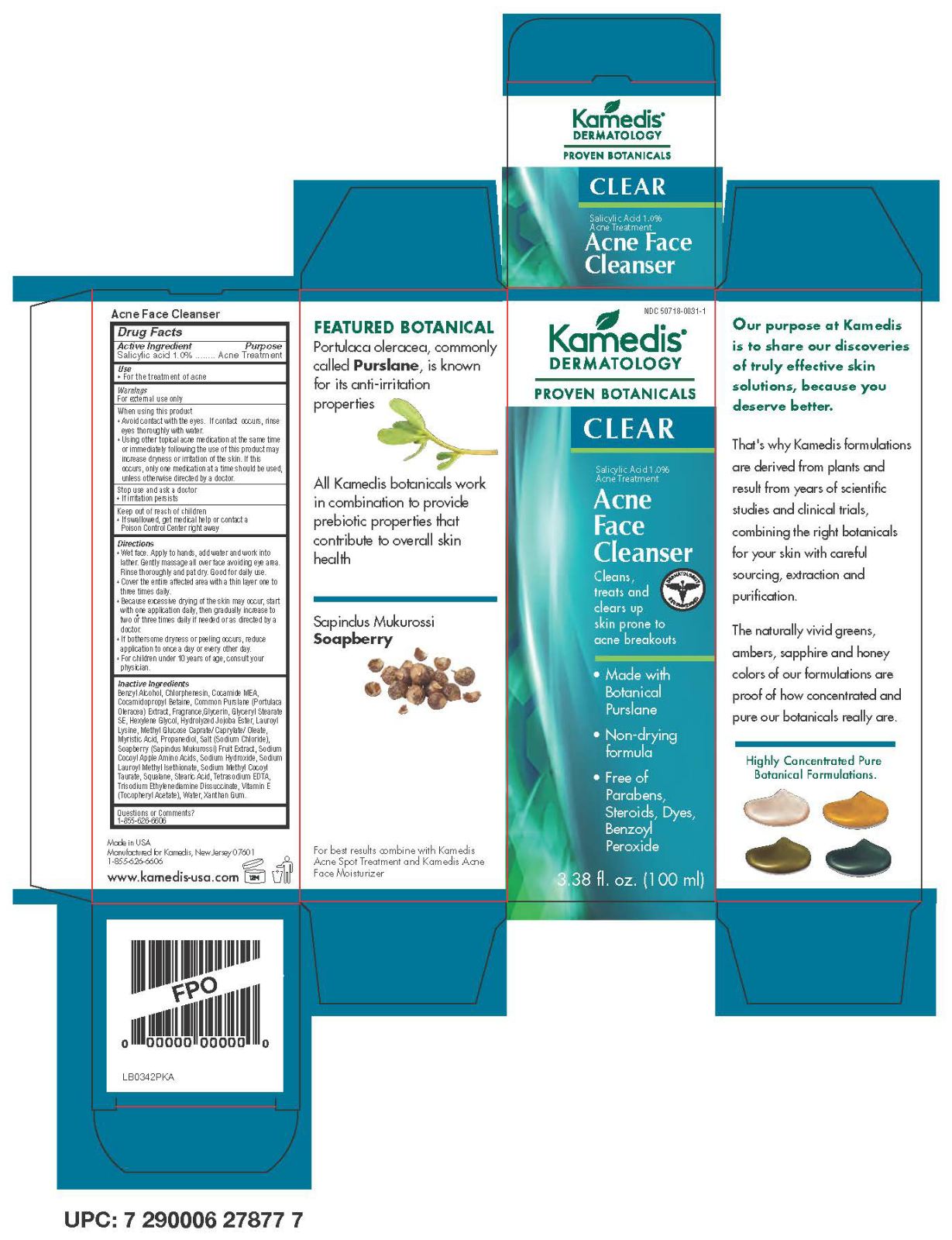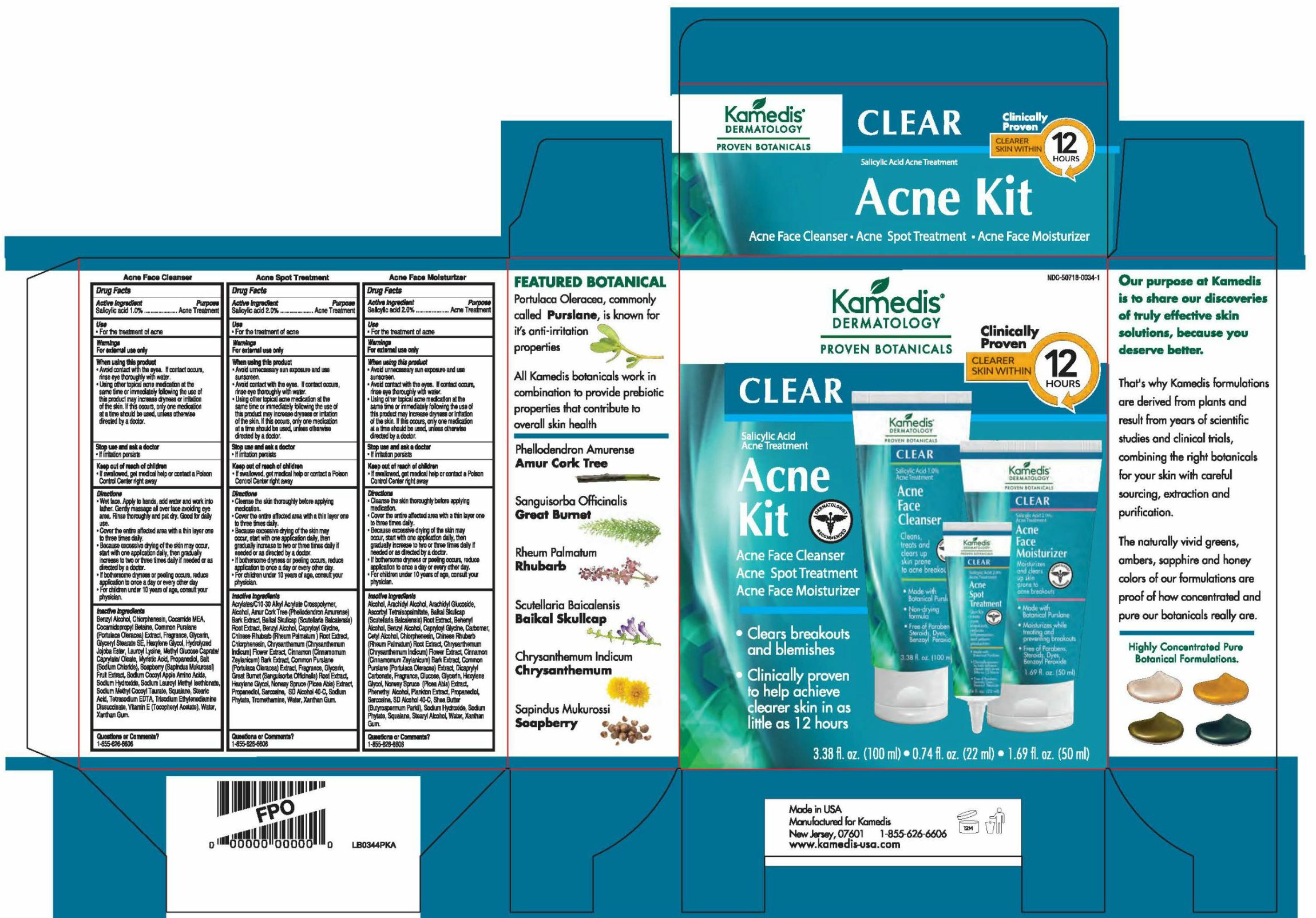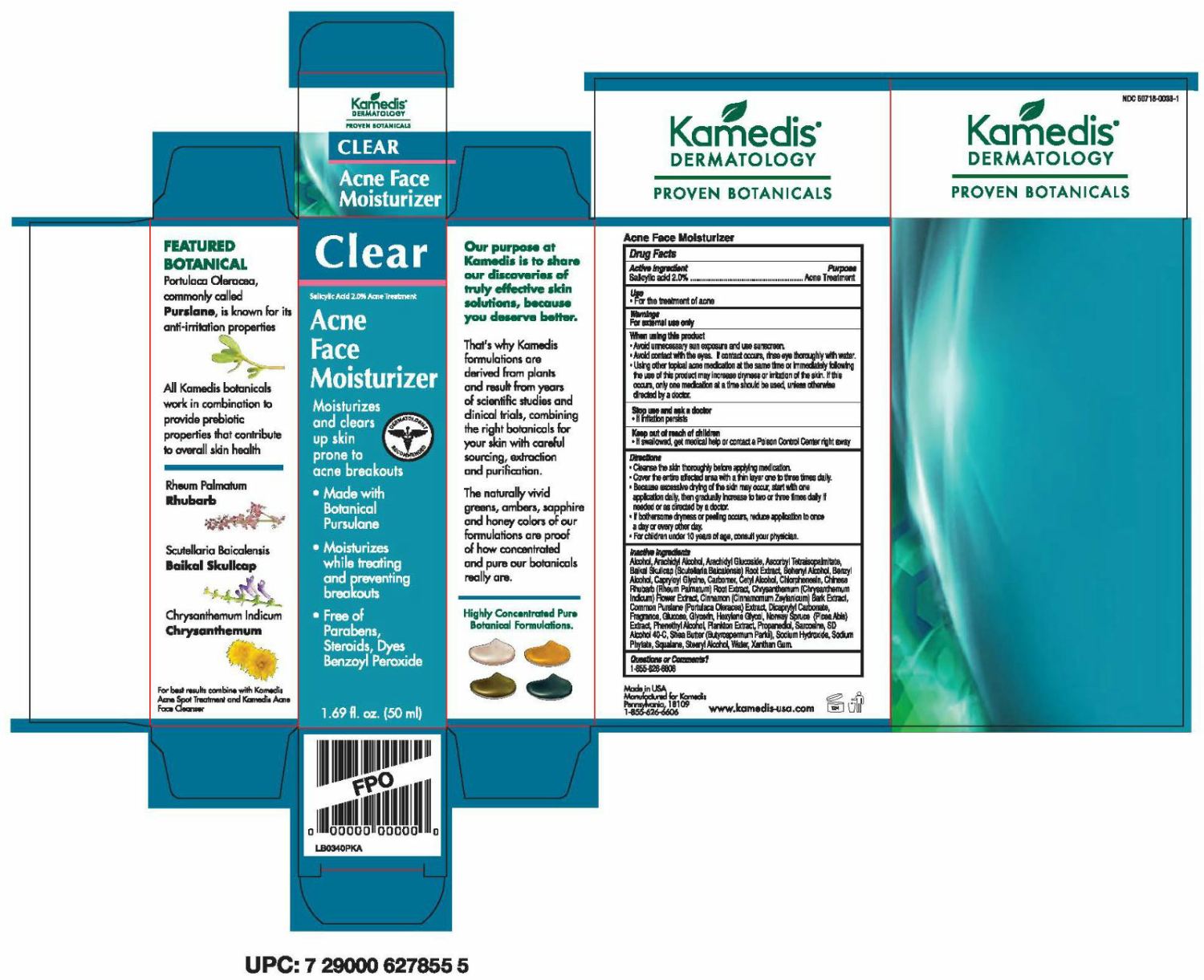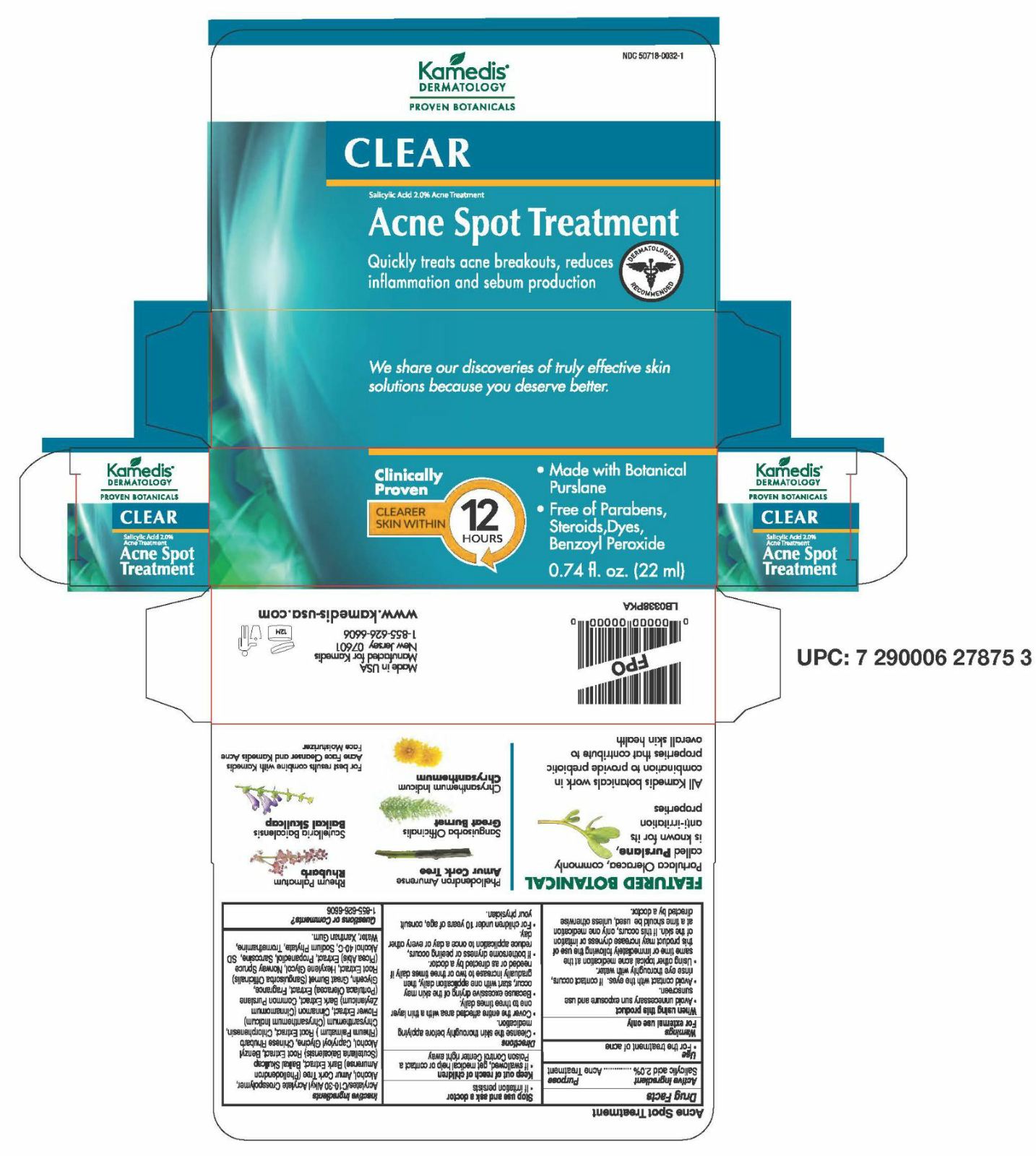 DRUG LABEL: Clear Acne Kit
NDC: 50718-0034 | Form: KIT | Route: TOPICAL
Manufacturer: Kamedis
Category: otc | Type: HUMAN OTC DRUG LABEL
Date: 20200706

ACTIVE INGREDIENTS: SALICYLIC ACID 14.4 mg/1 mL; SALICYLIC ACID 28.8 mg/1 mL; SALICYLIC ACID 28.8 mg/1 mL
INACTIVE INGREDIENTS: BENZYL ALCOHOL; PURSLANE; CHLORPHENESIN; GLYCERIN; HEXYLENE GLYCOL; PROPANEDIOL; WATER; XANTHAN GUM; SODIUM HYDROXIDE; SQUALANE; COCAMIDOPROPYL BETAINE; GLYCERYL STEARATE SE; COCO MONOETHANOLAMIDE; LAUROYL LYSINE; MYRISTIC ACID; SODIUM CHLORIDE; SAPINDUS MUKOROSSI FRUIT; SODIUM LAUROYL METHYL ISETHIONATE; SODIUM METHYL COCOYL TAURATE; STEARIC ACID; EDETATE SODIUM; TRISODIUM ETHYLENEDIAMINE DISUCCINATE; .ALPHA.-TOCOPHEROL ACETATE; HYDROLYZED JOJOBA ESTERS (ACID FORM); SODIUM COCOYL APPLE AMINO ACIDS; METHYL GLUCOSE; (C10-C30)ALKYL METHACRYLATE ESTER; ALCOHOL; PHELLODENDRON AMURENSE BARK; SCUTELLARIA BAICALENSIS ROOT; BENZYL ALCOHOL; CAPRYLOYL GLYCINE; CHLORPHENESIN; CHRYSANTHEMUM INDICUM FLOWER; PURSLANE; GLYCERIN; RHEUM PALMATUM ROOT; SANGUISORBA OFFICINALIS ROOT; PICEA ABIES WOOD; PROPANEDIOL; SARCOSINE; HEXASODIUM PHYTATE; TROMETHAMINE; WATER; XANTHAN GUM; CINNAMON BARK OIL; HEXYLENE GLYCOL; ARACHIDYL ALCOHOL; ALCOHOL; ARACHIDYL GLUCOSIDE; ASCORBYL TETRAISOPALMITATE; SCUTELLARIA BAICALENSIS ROOT; BENZYL ALCOHOL; CAPRYLOYL GLYCINE; CETYL ALCOHOL; PURSLANE; CHLORPHENESIN; RHEUM PALMATUM ROOT; CHRYSANTHEMUM INDICUM FLOWER; DICAPRYLYL CARBONATE; GLYCERIN; HEXYLENE GLYCOL; PICEA ABIES WOOD; PROPANEDIOL; SARCOSINE; WATER; XANTHAN GUM; CINNAMON BARK OIL; SHEA BUTTER; SODIUM HYDROXIDE; HEXASODIUM PHYTATE; SQUALANE; STEARYL ALCOHOL; DOCOSANOL; PHENYLETHYL ALCOHOL; CARBOMER INTERPOLYMER TYPE A (55000 CPS); DEXTROSE, UNSPECIFIED FORM; NORI

Clear Acne Kit

Step 1 - Acne Face Cleanser Drug Facts

Active Ingredient

Salicylic acid 1.0%

Purpose

Acne Treatment

Use

- For the treatment of acne

Warnings

For external use only

When using this product

- Avoid contact with the eyes. If contact occurs, rinse eyes thoroughly with water.
- Using other topical acne medication at the same time or immediately following the use of this product may increase dryness or irritation of the skin. If this occurs, only one medication at a time should be used, unless otherwise directed by a doctor.

Stop use and ask a doctor

- If irritation persists

Keep out of reach of children

- If swallowed, get medical help or contact a Poison Control Center right away.

Directions

- Wet face. Apply to hands, add water and work into lather. Gently massage all over face avoiding eye area. Rinse thoroughly and pat dry. Good for daily use.
- Cover the entire affected area with a thin layer one to three times daily.
- Because excessive drying of the skin may occur, start with one application daily, then gradually increase to two or three times daily if needed or as directed by a doctor.
- If bothersome dryness or peeling occurs, reduce application to once a day or every other day
- For children under 10 years of age, consult your physician.

Inactive Ingredients

Benzyl Alcohol, Chlorphenesin, Cocamide MEA, Cocamidopropyl Betaine, Common Purslane (Portulaca Oleracea) Extract, Fragrance, Glycerin, Glyceryl Stearate SE, Hexylene Glycol, Hydrolyzed Jojoba Ester, Lauroyl Lysine, Methyl Glucose Caprate/ Caprylate/ Oleate, Myristic Acid, Propanediol, Salt (Sodium Chloride), Soapberry (Sapindus Mukurossi) Fruit Extract, Sodium Cocoyl Apple Amino Acids, Sodium Hydroxide, Sodium Lauroyl Methyl Isethionate, Sodium Methyl Cocoyl Taurate, Squalane, Stearic Acid, Tetrasodium EDTA, Trisodium Ethylenediamine Dissuccinate, Vitamin E (Tocopheryl Acetate), Water, Xanthan Gum.

Questions or Comments?

1-855-626-6606

Step 2 - Acne Spot Treatment Drug Facts

Active Ingredient

Salicylic acid 2.0%

Purpose

Acne Treatment

Use

- For the treatment of acne

Warnings

For external use only

When using this product

- Avoid unnecessary sun exposure and use sunscreen.
- Avoid contact with the eyes. If contact occurs, rinse eyes thoroughly with water.
- Using other topical acne medication at the same time or immediately following the use of this product may increase dryness or irritation of the skin. If this occurs, only one medication at a time should be used, unless otherwise directed by a doctor.

Stop use and ask a doctor

- If irritation persists

Keep out of reach of children

- If swallowed, get medical help or contact a Poison Control Center right away.

Directions

- Cleanse the skin thoroughly before applying medication.
- Cover the entire affected area with a thin layer one to three times daily.
- Because excessive drying of the skin may occur, start with one application daily, then gradually increase to two or three times daily if needed or as directed by a doctor.
- If bothersome dryness or peeling occurs, reduce application to once a day or every other day.
- For children under 10 years of age, consult your physician.

Inactive Ingredients

Acrylates/C10-30 Alkyl Acrylate Crosspolymer, Alcohol, Amur Cork Tree (Phellodendron Amurense) Bark Extract, Baikal Skullcap (Scutellaria Baicalensis) Root Extract, Benzyl Alcohol, Capryloyl Glycine, Chinese Rhubarb (Rheum Palmatum) Root Extract, Chlorphenesin, Chrysanthemum (Chrysanthemum Indicum) Flower Extract, Cinnamon (Cinnamomum Zeylanicum) Bark Extract, Common Purslane (Portulaca Oleracea) Extract, Fragrance, Glycerin, Great Burnet (Sanguisorba Officinalis) Root Extract, Hexylene Glycol, Norway Spruce (Picea Abis) Extract, Propanediol, Sarcosine, SD Alcohol 40-C, Sodium Phytate, Tromethamine, Water, Xanthan Gum

Questions or Comments?

1-855-626-6606

Step 3 - Acne Face Moisturizer Drug Facts

Active Ingredient

Salicylic acid 2.0%

Purpose

Acne Treatment

Use

- For the treatment of acne

Warnings

For external use only

When using this product

- Avoid unnecessary sun exposure and use sunscreen.
- Avoid contact with the eyes. If contact occurs, rinse eyes thoroughly with water.
- Using other topical acne medication at the same time or immediately following the use of this product may increase dryness or irritation of the skin. If this occurs, only one medication at a time should be used, unless otherwise directed by a doctor.

Stop use and ask a doctor

- If irritation persists

Keep out of reach of children

- If swallowed, get medical help or contact a Poison Control Center right away.

Directions

- Cleanse the skin thoroughly before applying medication.
- Cover the entire affected area with a thin layer one to three times daily.
- Because excessive drying of the skin may occur, start with one application daily, then gradually increase to two or three times daily if needed or as directed by a doctor.
- If bothersome dryness or peeling occurs, reduce application to once a day or every other day.
- For children under 10 years of age, consult your physician.

Inactive Ingredients

Alcohol, Arachidyl Alcohol, Arachidyl Glucoside, Ascorbyl Tetraisopalmitate, Baikal Skullcap (Scutellaria Baicalensis) Root Extract, Behenyl Alcohol, Benzyl Alcohol, Capryloyl Glycine, Carbomer, Cetyl Alcohol, Chlorphenesin, Chinese Rhubarb (Rheum Palmatum) Root Extract, Chrysanthemum (Chrysanthemum Indicum) Flower Extract, Cinnamon (Cinnamomum Zeylanicum) Bark Extract, Common Purslane (Portulaca Oleracea) Extract, Dicaprylyl Carbonate, Fragrance, Glucose, Glycerin, Hexylene Glycol, Norway Spruce (Picea Abis) Extract, Phenethyl Alcohol, Plankton Extract, Propanediol, Sarcosine, SD Alcohol 40-C, Shea Butter (Butyrospermum Parkii), Sodium Hydroxide, Sodium Phytate, Squalane, Stearyl Alcohol, Water, Xanthan Gum.

Questions or Comments?

1-855-626-6606

Made in USA
Manufactured for Kamedis, New Jersey 07601
1-855-626-6606

www.kamedis-usa.com